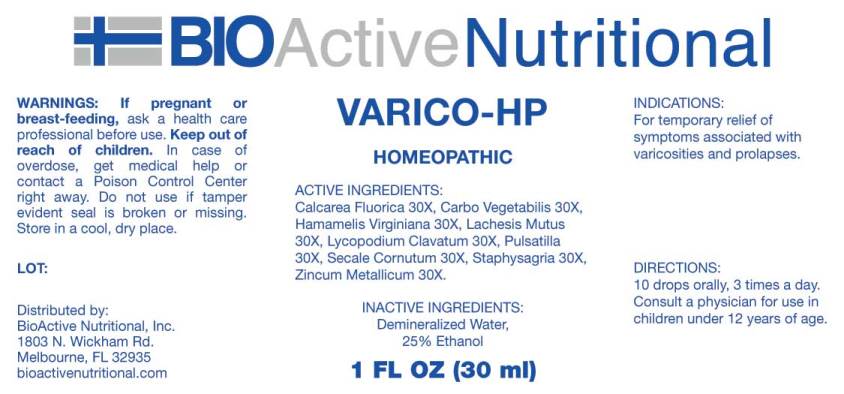 DRUG LABEL: VARICO HP
NDC: 43857-0341 | Form: LIQUID
Manufacturer: BioActive Nutritional, Inc.
Category: homeopathic | Type: HUMAN OTC DRUG LABEL
Date: 20180410

ACTIVE INGREDIENTS: CALCIUM FLUORIDE 30 [hp_X]/1 mL; ACTIVATED CHARCOAL 30 [hp_X]/1 mL; HAMAMELIS VIRGINIANA ROOT BARK/STEM BARK 30 [hp_X]/1 mL; LACHESIS MUTA VENOM 30 [hp_X]/1 mL; LYCOPODIUM CLAVATUM SPORE 30 [hp_X]/1 mL; ANEMONE PULSATILLA 30 [hp_X]/1 mL; CLAVICEPS PURPUREA SCLEROTIUM 30 [hp_X]/1 mL; DELPHINIUM STAPHISAGRIA SEED 30 [hp_X]/1 mL; ZINC 30 [hp_X]/1 mL
INACTIVE INGREDIENTS: WATER; ALCOHOL

Drug Facts:

ACTIVE INGREDIENTS:

Calcarea Fluorica 30X, Carbo Vegetabilis 30X, Hamamelis Virginiana 30X, Lachesis Mutus 30X, Lycopodium Clavatum 30X, Pulsatilla (Vulgaris) 30X, Secale Cornutum 30X, Staphysagria 30X, Zincum Metallicum 30X

INDICATIONS:

For temporary relief of symptoms associated varicosities and prolapses.

WARNINGS:

If pregnant or breast-feeding, ask a health care professional before use.

Keep out of reach of children. In case of overdose, get medical help or contact a Poison Control Center right away.

Do not use if tamper evident seal is broken or missing. Store in a cool, dry place.

Keep out of reach of children. In case of overdose, get medical help or contact a Poison Control Center right away.

DIRECTIONS:

10 drops orally, 3 times a day. Consult a physician for use in children under 12 years of age.

INDICATIONS:

For temporary relief of symptoms associated varicosities and prolapses.

INACTIVE INGREDIENTS:

Demineralized Water, 25% Ethanol

QUESTIONS:

Distributed by:

BioActive Nutritional, Inc.

1803 N. Wickham Rd.

Melbourne, FL 32935

bioactivenutritional.com

PACKAGE LABEL DISPLAY:

BIOActive Nutritional

VARICO-HP

HOMEOPATHIC

1 FL OZ (30 ml)